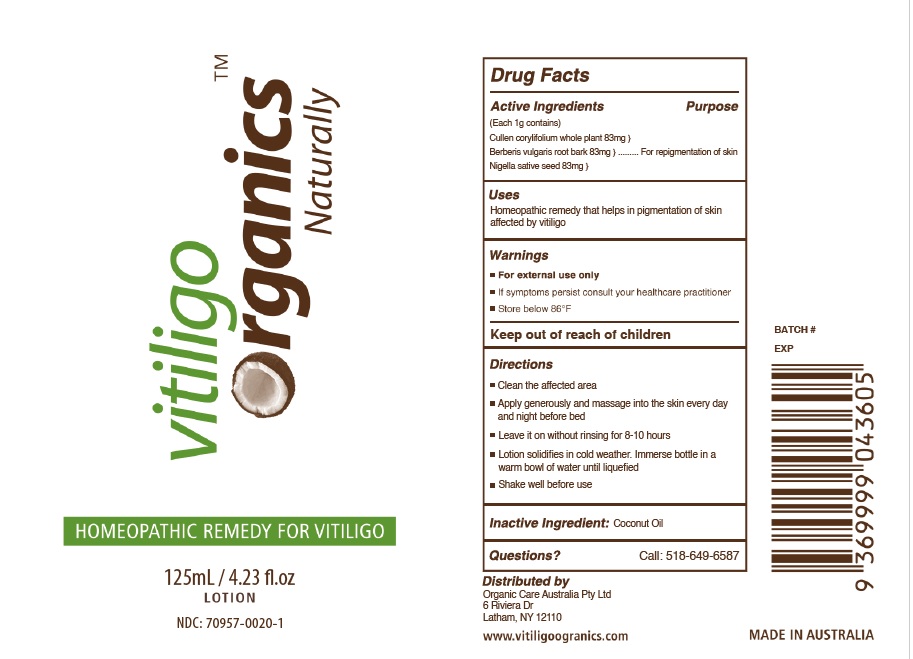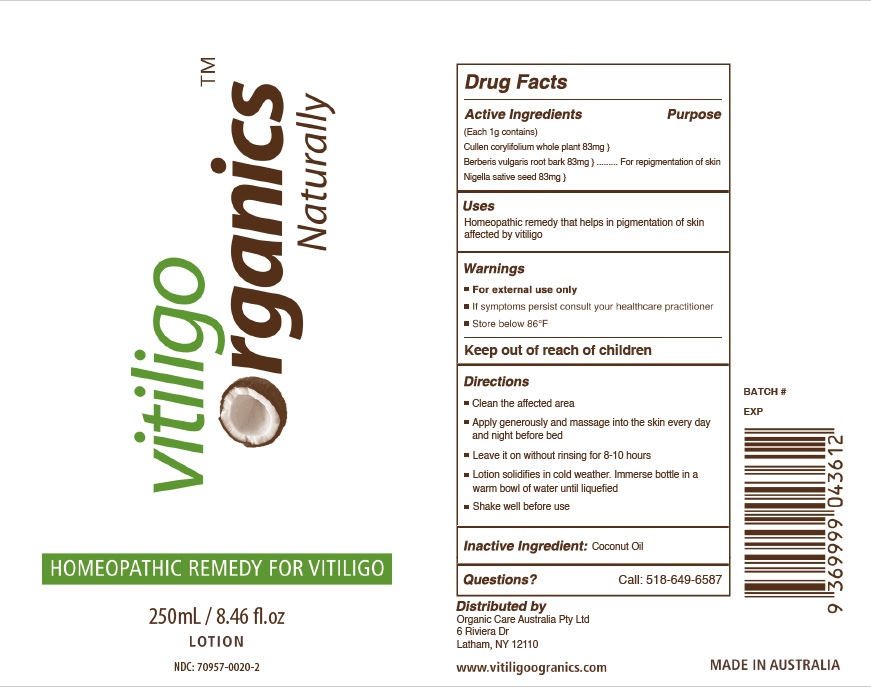 DRUG LABEL: Vitiligo Organics
NDC: 70957-0020 | Form: OINTMENT
Manufacturer: Organic Care Australia Pty LTD
Category: homeopathic | Type: HUMAN OTC DRUG LABEL
Date: 20251017

ACTIVE INGREDIENTS: CULLEN CORYLIFOLIUM WHOLE 83 mg/125 mL; NIGELLA SATIVA SEED 83 mg/125 mL; BERBERIS VULGARIS ROOT BARK 83 mg/125 mL
INACTIVE INGREDIENTS: COCONUT OIL 752 mg/125 mL

Homeopathic Remedy for Vitiligo

Actives

Each 1g contains:

Cullen corylifolium whole plant...83mg

Berberis vulgaris root bark...83mg

Nigella sativa seed...83mg

Purpose

For repigmentation of skin

Keep out of reach of children

Warnings

• For external use only
• If symptoms persist consult your healthcare practitioner
• Store below 86oF

Directions

Clean the affected area Apply generously and massage into the skin every day and night before bed Leave it on without rinsing for 8-10 hours Lotion solidifies in cold weather.

Immerse bottle in a warm bowl of water until liquefied Shake well before use

Usage

Homeopathic remedy that helps in pigmentation of skin affected by vitiligo.

Inactives

Coconut Oil